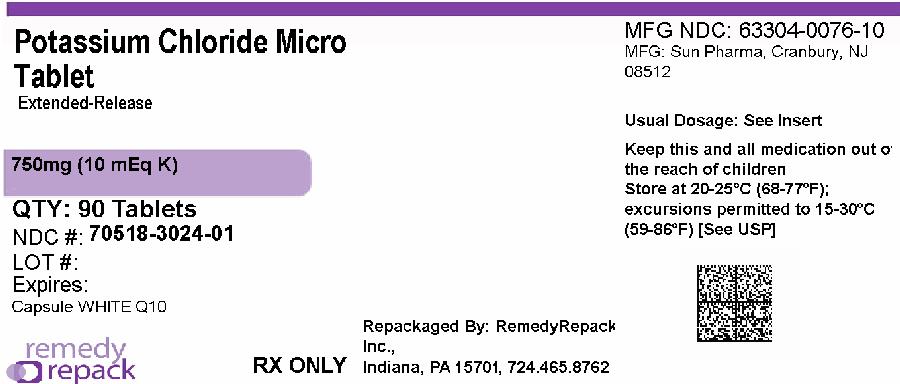 DRUG LABEL: Potassium Chloride Extended-Release
NDC: 70518-3024 | Form: TABLET, EXTENDED RELEASE
Manufacturer: REMEDYREPACK INC.
Category: prescription | Type: HUMAN PRESCRIPTION DRUG LABEL
Date: 20260217

ACTIVE INGREDIENTS: POTASSIUM CHLORIDE 750 mg/1 1
INACTIVE INGREDIENTS: SILICON DIOXIDE; CROSPOVIDONE, UNSPECIFIED; DIETHYL PHTHALATE; ETHYLCELLULOSE, UNSPECIFIED; MICROCRYSTALLINE CELLULOSE

POTASSIUM CHLORIDE EXTENDED RELEASE TABLETS, USP 10 mEq K

DESCRIPTION

The Potassium Chloride Extended Release Tablets, USP, 10 mEq product is an immediately dispersing extended release oral dosage form of potassium chloride containing 750 mg of microencapsulated potassium chloride, USP equivalent to 10 mEq of potassium in a tablet.

These formulations are intended to slow the release of potassium so that the likelihood of a high localized concentration of potassium chloride within the gastrointestinal tract is reduced.

Potassium Chloride Extended Release Tablets, USP, 10mEq are an electrolyte replenisher. The chemical name of the active ingredient is potassium chloride, and the structural formula is KCl. Potassium chloride, USP occurs as a white, granular powder or as colorless crystals. It is odorless and has a saline taste. Its solutions are neutral to litmus. It is freely soluble in water and insoluble in alcohol.

Potassium Chloride Extended Release Tablets, USP, 10mEq are a tablet formulation (not enteric coated or wax matrix) containing individually microencapsulated potassium chloride crystals which disperse upon tablet disintegration.

In simulated gastric fluid at 37°C and in the absence of outside agitation, Potassium Chloride Extended Release Tablets, USP, 10 mEq begin disintegrating into micro-encapsulated crystals within seconds and completely disintegrates within 1 minute. The microencapsulated crystals are formulated to provide an extended release of potassium chloride.

FDA approved dissolution test specifications differ from USP.

Inactive Ingredients:Colloidal silicon dioxide, crospovidone, diethyl phthalate, ethylcellulose, microcrystalline cellulose.

CLINICAL PHARMACOLOGY

The potassium ion is the principal intracellular cation of most body tissues. Potassium ions participate in a number of essential physiological processes including the maintenance of intracellular tonicity; the transmission of nerve impulses; the contraction of cardiac, skeletal, and smooth muscle; and the maintenance of normal renal function.

The intracellular concentration of potassium is approximately 150 to 160 mEq per liter. The normal adult plasma concentration is 3.5 to 5 mEq per liter. An active ion transport system maintains this gradient across the plasma membrane.

Potassium is a normal dietary constituent and under steady-state conditions the amount of potassium absorbed from the gastrointestinal tract is equal to the amount excreted in the urine. The usual dietary intake of potassium is 50 to 100 mEq per day.

Potassium depletion will occur whenever the rate of potassium loss through renal excretion and/or loss from the gastrointestinal tract exceeds the rate of potassium intake. Such depletion usually develops as a consequence of therapy with diuretics, primary or secondary hyperaldosteronism, diabetic ketoacidosis, or inadequate replacement of potassium in patients on prolonged parenteral nutrition. Depletion can develop rapidly with severe diarrhea, especially if associated with vomiting.

Potassium depletion due to these causes is usually accompanied by a concomitant loss of chloride and is manifested by hypokalemia and metabolic alkalosis.

Potassium depletion may produce weakness, fatigue, disturbances or cardiac rhythm (primarily ectopic beats), prominent U-waves in the electrocardiogram, and in advanced cases, flaccid paralysis and/or impaired ability to concentrate urine.

If potassium depletion associated with metabolic alkalosis cannot be managed by correcting the fundamental cause of the deficiency, e.g. where the patient requires long-term diuretic therapy, supplemental potassium in the form of high potassium food or potassium chloride may be able to restore normal potassium levels.

In rare circumstances (e.g. patients with renal tubular acidosis) potassium depletion may be associated with metabolic acidosis and hyperchloremia. In such patients potassium replacement should be accomplished with potassium salts other than the chloride, such as potassium bicarbonate, potassium citrate, potassium acetate, or potassium gluconate.

INDICATIONS AND USAGE

BECAUSE OF REPORTS OF INTESTINAL AND GASTRIC ULCERATION AND BLEEDING WITH CONTROLLED RELEASE POTASSIUM CHLORIDE PREPARATIONS, THESE DRUGS SHOULD BE RESERVED FOR THOSE PATIENTS WHO CANNOT TOLERATE OR REFUSE TO TAKE LIQUID OR EFFERVESCENT POTASSIUM PREPARATIONS OR FOR PATIENTS IN WHOM THERE IS A PROBLEM OF COMPLIANCE WITH THESE PREPARATIONS.

1. For the treatment of patients with hypokalemia with or without metabolic alkalosis, in digitalis intoxication, and in patients with hypokalemic familial periodic paralysis. If hypokalemia is the result of diuretic therapy, consideration should be given to the use of a lower dose of diuretic, which may be sufficient without leading to hypokalemia.
2. For the prevention of hypokalemia in patients who would be at particular risk if hypokalemia were to develop, e.g. digitalized patients or patients with significant cardiac arrhythmias.

The use of potassium salts in patients receiving diuretics for uncomplicated essential hypertension is often unnecessary when such patients have a normal dietary pattern and when low doses of the diuretic are used. Serum potassium should be checked periodically, however, and if hypokalemia occurs, dietary supplementation with potassium-containing foods may be adequate to control milder cases. In more severe cases, and if dose adjustment of the diuretic is ineffective or unwarranted, supplementation with potassium salts may be indicated.

CONTRAINDICATIONS

Potassium supplements are contraindicated in patients with hyperkalemia since a further increase in serum potassium concentration in such patients can produce cardiac arrest. Hyperkalemia may complicate any of the following conditions: chronic renal failure, systemic acidosis, such as diabetic acidosis, acute dehydration, extensive tissue breakdown as in severe burns, adrenal insufficiency, or the administration of a potassium-sparing diuretic (e.g. spironolactone, triamterene, amiloride) (see OVERDOSAGE).

Controlled-release formulations of potassium chloride have produced esophageal ulceration in certain cardiac patients with esophageal compression due to enlarged left atrium. Potassium supplementation, when indicated in such patients, should be given as a liquid preparation or as an aqueous (water) suspension of Potassium Chloride (see PRECAUTIONS: Information for Patients, and DOSAGE AND ADMINISTRATIONsections).

All solid oral dosage forms of potassium chloride are contraindicated in any patient in whom there is structural, pathological (e.g. diabetic gastroparesis), or pharmacologic (use of anticholinergic agents or other agents with anticholinergic properties at sufficient doses to exert anticholinergic effects) cause for arrest or delay in tablet passage through the gastrointestinal tract.

WARNINGS

Hyperkalemia (see OVERDOSAGE): In patients with impaired mechanisms for excreting potassium, the administration of potassium salts can produce hyperkalemia and cardiac arrest. This occurs most commonly in patients given potassium by the intravenous route but may also occur in patients given potassium orally. Potentially fatal hyperkalemia can develop rapidly and be asymptomatic. The use of potassium salts in patients with chronic renal disease, or any other condition which impairs potassium excretion, requires particularly careful monitoring of the serum potassium concentration and appropriate dosage adjustment.

Interaction with Potassium-Sparing Diuretics: Hypokalemia should not be treated by the concomitant administration of potassium salts and a potassium-sparing diuretic (e.g. spironolactone, triamterene, or amiloride) since the simultaneous administration of these agents can produce severe hyperkalemia.

Interaction with Renin-Angiotensin-Aldosterone System Inhibitors:Drugs that inhibit the renin-angiotensin aldosterone system (RAAS) including angiotensin converting enzyme (ACE) inhibitors, angiotensin receptor blockers (ARBs), spironolactone, eplerenone, or aliskiren produce potassium retention by inhibiting aldosterone production. Closely monitor potassium in patients receiving concomitant RAAS therapy.

Interaction with Nonsteroidal Anti-Inflammatory Drugs:Nonsteroidal anti-inflammatory drugs (NSAIDs) may produce potassium retention by reducing renal synthesis of prostaglandin E and impairing the renin-angiotensin system. Closely monitor potassium in patients receiving concomitant NSAID therapy.

Gastrointestinal Lesions: Solid oral dosage forms of potassium chloride can produce ulcerative and/or stenotic lesions of the gastrointestinal tract. Based on spontaneous adverse reaction reports, enteric-coated preparations of potassium chloride are associated with an increased frequency of small bowel lesions (40-50 per 100,000 patient years) compared to sustained release wax matrix formulations (less than one per 100,000 patient years). Because of the lack of extensive marketing experience with microencapsulated products, a comparison between such products and wax matrix or enteric-coated products is not available. Potassium Chloride Extended Release Tablets, USP, 10 mEq are tablets formulated to provide a controlled rate of release of microencapsulated potassium chloride and thus to minimize the possibility of a high local concentration of potassium near the gastrointestinal wall.

Prospective trials have been conducted in normal human volunteers in which the upper gastrointestinal tract was evaluated by endoscopic inspection before and after 1 week of solid oral potassium chloride therapy. The ability of this model to predict events occurring in usual clinical practice is unknown. Trials which approximated usual clinical practice did not reveal any clear differences between the wax matrix and microencapsulated dosage forms. In contrast, there was a higher incidence of gastric and duodenal lesions in subjects receiving a high dose of a wax matrix controlled-release formulation under conditions which did not resemble usual or recommended clinical practice (i.e. 96mEq per day in divided doses of potassium chloride administered to fasted patients, in the presence of an anticholinergic drug to delay gastric emptying). The upper gastrointestinal lesions observed by endoscopy were asymptomatic and were not accompanied by evidence of bleeding (Hemoccult testing). The relevance of these findings to the usual conditions (i.e., non-fasting, no anticholinergic agent, smaller doses) under which controlled release potassium chloride products are used is uncertain; epidemiologic studies have not identified an elevated risk, compared to microencapsulated products, for upper gastrointestinal lesions in patients receiving wax matrix formulations. Potassium Chloride Extended Release Tablets, USP, 10 mEq should be discontinued immediately and the possibility of ulceration, obstruction, or perforation should be considered if severe vomiting, abdominal pain, distention, or gastrointestinal bleeding occurs.

Metabolic Acidosis:Hypokalemia in patients with metabolic acidosis should be treated with an alkalinizing potassium salt such as potassium bicarbonate, potassium citrate, potassium acetate, or potassium gluconate.

PRECAUTIONS

General

The diagnosis of potassium depletion is ordinarily made by demonstrating hypokalemia in a patient with a clinical history suggesting some cause for potassium depletion. In interpreting the serum potassium level, the physician should bear in mind that acute alkalosis per se can produce hypokalemia in the absence of a deficit in total body potassium while acute acidosis per se can increase the serum potassium concentration into the normal range even in the presence of a reduced total body potassium. The treatment of potassium depletion, particularly in the presence of cardiac disease, renal disease, or acidosis requires careful attention to acid-base balance and appropriate monitoring of serum electrolytes, the electrocardiogram, and the clinical status of the patient.

Information for Patients

Physicians should consider reminding the patient of the following:

To take each dose with meals and with a full glass of water or other liquid.

To take each dose without crushing, chewing, or sucking the tablets. If those patients are having difficulty swallowing whole tablets, they may try one of the following alternate methods of administration:

1. Break the tablet in half, and take each half separately with a glass of water.
2. Prepare an aqueous (water) suspension as follows:
  1. Place the whole tablet(s) in approximately 1/2 glass of water (4 fluid ounces).
  2. Allow approximately 2 minutes for the tablet(s) to disintegrate.
  3. Stir for about half a minute after the tablet(s) has disintegrated.
  4. Swirl the suspension and consume the entire contents of the glass immediately by drinking or by the use of a straw.
  5. Add another 1 fluid ounce of water, swirl, and consume immediately.
  6. Then, add an additional 1 fluid ounce of water, swirl, and consume immediately.

Aqueous suspension of Potassium Chloride that is not taken immediately should be discarded. The use of other liquids for suspending Potassium Chloride Extended Release Tablets, USP, 10 mEq is not recommended.

To take this medicine following the frequency and amount prescribed by the physician. This is especially important if the patient is also taking diuretics and/or digitalis preparations.

To check with the physician at once if tarry stools or other evidence of gastrointestinal bleeding is noticed.

Repackaged By / Distributed By: RemedyRepack Inc.

625 Kolter Drive, Indiana, PA 15701

(724) 465-8762

Laboratory Tests

When blood is drawn for analysis of plasma potassium it is important to recognize that artifactual elevations can occur after improper venipuncture technique or as a result of in vitrohemolysis of the sample.

Drug Interactions

Potassium-sparing diuretics, angiotensin-converting enzyme inhibitors (see WARNINGS).

Carcinogenesis, Mutagenesis, Impairment of Fertility

Carcinogenicity, mutagenicity, and fertility studies in animals have not been performed. Potassium is a normal dietary constituent.

Pregnancy

Animal reproduction studies have not been conducted with Potassium Chloride Extended Release Tablets, USP, 10 mEq. It is unlikely that potassium supplementation that does not lead to hyperkalemia would have an adverse effect on the fetus or would affect reproductive capacity.

Nursing Mothers

The normal potassium ion content of human milk is about 13 mEq per liter. Since oral potassium becomes part of the body potassium pool, so long as body potassium is not excessive, the contribution of potassium chloride supplementation should have little or no effect on the level in human milk.

Pediatric Use

Safety and effectiveness in pediatric patients have not been established.

Geriatric Use

Clinical studies of Potassium Chloride Extended Release Tablets, USP, 10 mEq did not include sufficient numbers of subjects aged 65 and over to determine whether they respond differently from younger subjects. Other reported clinical experience has not identified differences in responses between the elderly and younger patients. In general, dose selection for an elderly patient should be cautious, usually starting at the low end of the dosing range, reflecting the greater frequency of decreased hepatic, renal or cardiac function, and of concomitant disease or other drug therapy.

This drug is known to be substantially excreted by the kidney, and the risk of toxic reactions to this drug may be greater in patients with impaired renal function. Because elderly patients are more likely to have decreased renal function, care should be taken in dose selection; and it may be useful to monitor renal function.

ADVERSE REACTIONS

One of the most severe adverse effects is hyperkalemia (see CONTRAINDICATIONS, WARNINGS, and OVERDOSAGE).

There have also been reports of upper and lower gastrointestinal conditions including obstruction, bleeding, ulceration, and perforation (see CONTRAINDICATIONSand WARNINGS). The most common adverse reactions to oral potassium salts are nausea, vomiting, flatulence, abdominal pain/discomfort, and diarrhea. These symptoms are due to irritation of the gastrointestinal tract and are best managed by diluting the preparation further, taking the dose with meals or reducing the amount taken at one time.

Call your doctor for medical advice about side effects.

To report SUSPECTED ADVERSE REACTIONS, contact the manufacturer Adare at 1-877-731-5116 or FDA at 1-800-FDA-1088 or www.fda.gov/medwatch.

OVERDOSAGE

The administration of oral potassium salts to persons with normal excretory mechanisms for potassium rarely causes serious hyperkalemia. However, if excretory mechanisms are impaired or if potassium is administered too rapidly intravenously, potentially fatal hyperkalemia can result (see CONTRAINDICATIONSand WARNINGS). It is important to recognize that hyperkalemia is usually asymptomatic and may be manifested only by an increased serum potassium concentration (6.5-8.0 mEq/L) and characteristic electrocardiographic changes (peaking of T-waves, loss of P-waves, depression of S-T segment and prolongation of the QT-interval).

Late manifestations include muscle paralysis and cardiovascular collapse from cardiac arrest (9-12 mEq/L).

Treatment measures for hyperkalemia include the following:

1. Patients should be closely monitored for arrhythmias and electrolyte changes.
2. Elimination of foods and medications containing potassium and of any agents with potassium-sparing properties such as potassium-sparing diuretics, ARBS, ACE inhibitors, NSAIDS, certain nutritional supplements and many others.
3. Intravenous calcium gluconate if the patient is at no risk or low risk of developing digitalis toxicity.
4. Intravenous administration of 300 to 500 mL/hr of 10% dextrose solution containing 10-20 units of crystalline insulin per 1,000 mL.
5. Correction of acidosis, if present, with intravenous sodium bicarbonate.
6. Use of exchange resins, hemodialysis, or peritoneal dialysis.

In treating hyperkalemia, it should be recalled that in patients who have been stabilized on digitalis, too rapid a lowering of the serum potassium concentration can produce digitalis toxicity.

The extended release feature means that absorption and toxic effects may be delayed for hours.

Consider standard measures to remove any unabsorbed drug.

DOSAGE AND ADMINISTRATION

The usual dietary intake of potassium by the average adult is 50 to 100 mEq per day. Potassium depletion sufficient to cause hypokalemia usually requires the loss of 200 or more mEq of potassium from the total body store.

Dosage must be adjusted to the individual needs of each patient. The dose for the prevention of hypokalemia is typically in the range of 20 mEq per day. Doses of 40-100 mEq per day or more are used for the treatment of potassium depletion. Dosage should be divided if more than 20 mEq per day is given such that no more than 20 mEq is given in a single dose.

Each Potassium Chloride Extended Release Tablet, USP, 10 mEq provides 10 mEq of potassium chloride.

Potassium Chloride Extended Release Tablets, USP, 10mEq should be taken with meals and with a glass of water or other liquid. This product should not be taken on an empty stomach because of its potential for gastric irritation (see WARNINGS).

Patients having difficulty swallowing whole tablets may try one of the following alternate methods of administration:

1. Break the tablet in half, and take each half separately with a glass of water.
2. Prepare an aqueous (water) suspension as follows:
  1. Place the whole tablet(s) in approximately 1/2 glass of water (4 fluid ounces).
  2. Allow approximately 2 minutes for the tablet(s) to disintegrate.
  3. Stir for about half a minute after the tablet(s) has disintegrated.
  4. Swirl the suspension and consume the entire contents of the glass immediately by drinking or by the use of a straw.
  5. Add another 1 fluid ounce of water, swirl, and consume immediately.
  6. Then, add an additional 1 fluid ounce of water, swirl, and consume immediately.

Aqueous suspension of Potassium Chloride Extended Release Tablets, USP, 10mEq that is not taken immediately should be discarded. The use of other liquids for suspending Potassium Chloride Extended Release Tablets, USP, 10mEq is not recommended.

HOW SUPPLIED

Potassium Chloride Extended Release Tablets, USP, 10mEq are capsule shaped, white to off-white tablets, with “Q10” imprinted on one side and plain on the other side.

NDC: 70518-3024-00

NDC: 70518-3024-01

PACKAGING: 30 in 1 BLISTER PACK

PACKAGING: 90 in 1 BOTTLE PLASTIC

Storage Conditions: Keep tightly closed. Store at 25°C (77°F); excursions permitted to 15° to 30°C (59° to 86°F) [see USP Controlled Room Temperature].

Repackaged and Distributed By:

Remedy Repack, Inc.

625 Kolter Dr. Suite #4 Indiana, PA 1-724-465-8762

PRINCIPAL DISPLAY PANEL

DRUG: Potassium Chloride Extended-Release

GENERIC: Potassium Chloride

DOSAGE: TABLET, EXTENDED RELEASE

ADMINSTRATION: ORAL

NDC: 70518-3024-0

NDC: 70518-3024-1

COLOR: white

SHAPE: CAPSULE

SCORE: No score

SIZE: 17 mm

IMPRINT: Q10

PACKAGING: 30 in 1 BLISTER PACK

PACKAGING: 90 in 1 BOTTLE PLASTIC

ACTIVE INGREDIENT(S):

- POTASSIUM CHLORIDE 750mg in 1

INACTIVE INGREDIENT(S):

- SILICON DIOXIDE
- CROSPOVIDONE, UNSPECIFIED
- DIETHYL PHTHALATE
- ETHYLCELLULOSE, UNSPECIFIED
- MICROCRYSTALLINE CELLULOSE